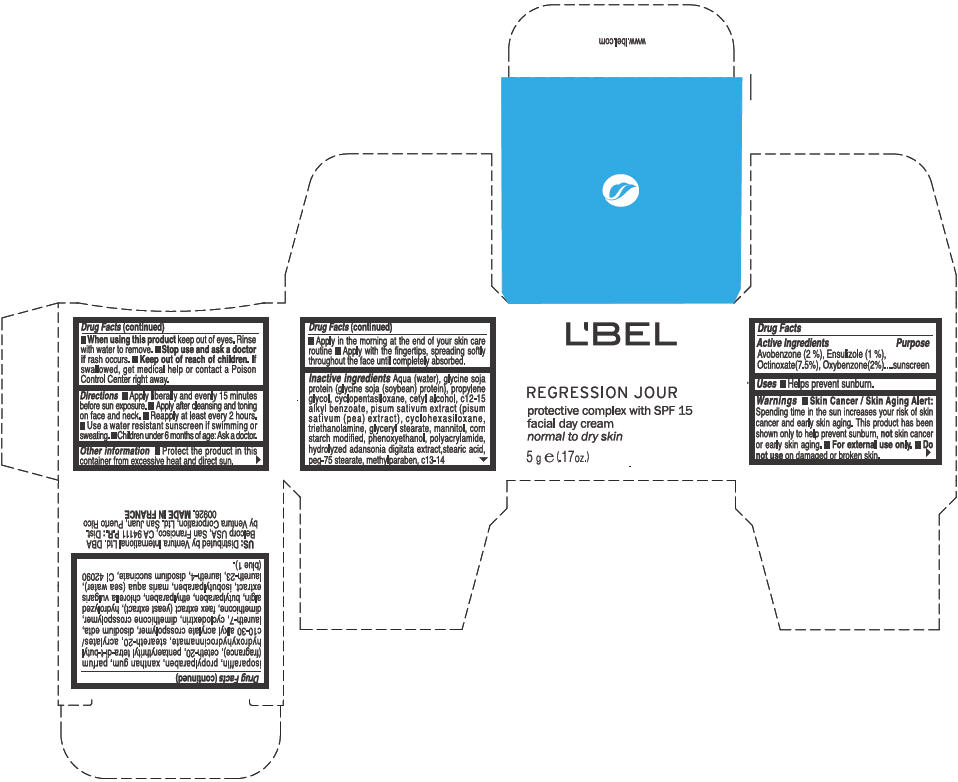 DRUG LABEL: LBEL REGRESSION JOUR 
NDC: 14783-025 | Form: CREAM
Manufacturer: Ventura International Ltd.
Category: otc | Type: HUMAN OTC DRUG LABEL
Date: 20120521

ACTIVE INGREDIENTS: Avobenzone 0.02 g/1 g; Ensulizole 0.01 g/1 g; Octinoxate 0.075 g/1 g; Oxybenzone 0.02 g/1 g
INACTIVE INGREDIENTS: WATER; PROPYLENE GLYCOL; CYCLOMETHICONE 5; CETYL ALCOHOL; ALKYL (C12-15) BENZOATE; PEA; CYCLOMETHICONE 6; TROLAMINE; GLYCERYL MONOSTEARATE; MANNITOL; PHENOXYETHANOL; STEARIC ACID; PEG-75 STEARATE; METHYLPARABEN; C13-14 ISOPARAFFIN; PROPYLPARABEN; XANTHAN GUM; CETETH-20; PENTAERYTHRITOL TETRAKIS(3-(3,5-DI-TERT-BUTYL-4-HYDROXYPHENYL)PROPIONATE); STEARETH-20; EDETATE DISODIUM; LAURETH-7; DIMETHICONE; YEAST; BUTYLPARABEN; ETHYLPARABEN; CHLORELLA VULGARIS; ISOBUTYLPARABEN; LAURETH-23; LAURETH-4; SODIUM SUCCINATE ANHYDROUS; FD&C BLUE NO. 1

L'BEL REGRESSION JOUR
Protective Complex with SPF 15 Facial day normal to dry skin

Drug Facts

ACTIVE INGREDIENT

Active Ingredients | Purpose
Avobenzone (2 %) | Sunscreen
Ensulizole (1 %) | Sunscreen
Octinoxate (7.5 %) | Sunscreen
Oxybenzone (2 %) | Sunscreen

Uses

- Helps prevent sunburn.

Warnings

- Skin Cancer / Skin Aging Alert: Spending time in the sun increases your risk of skin cancer and early skin aging. This product has been shown only to help prevent sunburn, not skin cancer or early skin aging.

WHEN USING

- For external use only.

- Do not use on damaged or broken skin.

- When using this product keep out of eyes. Rinse with water to remove.

- Stop use and ask a doctor if rash occurs.

- Keep out of reach of children. If swallowed, get medical help or contact a Poison Control Center right away.

Directions

- Apply liberally and evenly 15 minutes before sun exposure.
- Apply after cleansing and toning on face and neck
- Reapply at least every 2 hours
- Use a water resistant sunscreen if swimming or sweating.
- Children under 6 months of age: Ask a doctor

Other information

- Protect the product in this container from excessive heat and direct sun.
- Apply in the morning at the end of your skin care routine
- Apply with the fingertips, spreading softly throughout the face until
  completely absorbed

Inactive ingredients

Aqua (water), glycine soja protein (glycine soja (soybean) protein), propylene glycol, cyclopentasiloxane, cetyl alcohol, c12-15 alkyl benzoate, pisum sativum extract (pisum sativum (pea) extract), cyclohexasiloxane, triethanolamine, glyceryl stearate, mannitol, corn starch modified, phenoxyethanol, polyacrylamide, hydrolyzed adansonia digitata extract,stearic acid, peg-75 stearate, methylparaben, c13-14 isoparaffin, propylparaben, xanthan gum, parfum (fragrance), ceteth-20, pentaerythrityl tetra-di-t-butyl hydroxyhydrocinnamate, steareth-20, acrylates/c10-30 alkyl acrylate crosspolymer, disodium edta, laureth-7, cyclodextrin, dimethicone crosspolymer, dimethicone, faex extract (yeast extract), hydrolyzed algin, butylparaben, ethylparaben, chlorella vulgaris extract, isobutylparaben, maris aqua (sea water), laureth-23, laureth-4, disodium succinate, CI 42090 (blue 1)

US: Distributed by Ventura International Ltd. DBA Belcorp USA, San Francisco, CA 94111

PRINCIPAL DISPLAY PANEL - 5 g Jar Box

L'BEL

REGRESSION JOUR

protective complex with SPF 15
facial day cream
normal to dry skin

5 g e (.17 oz.)